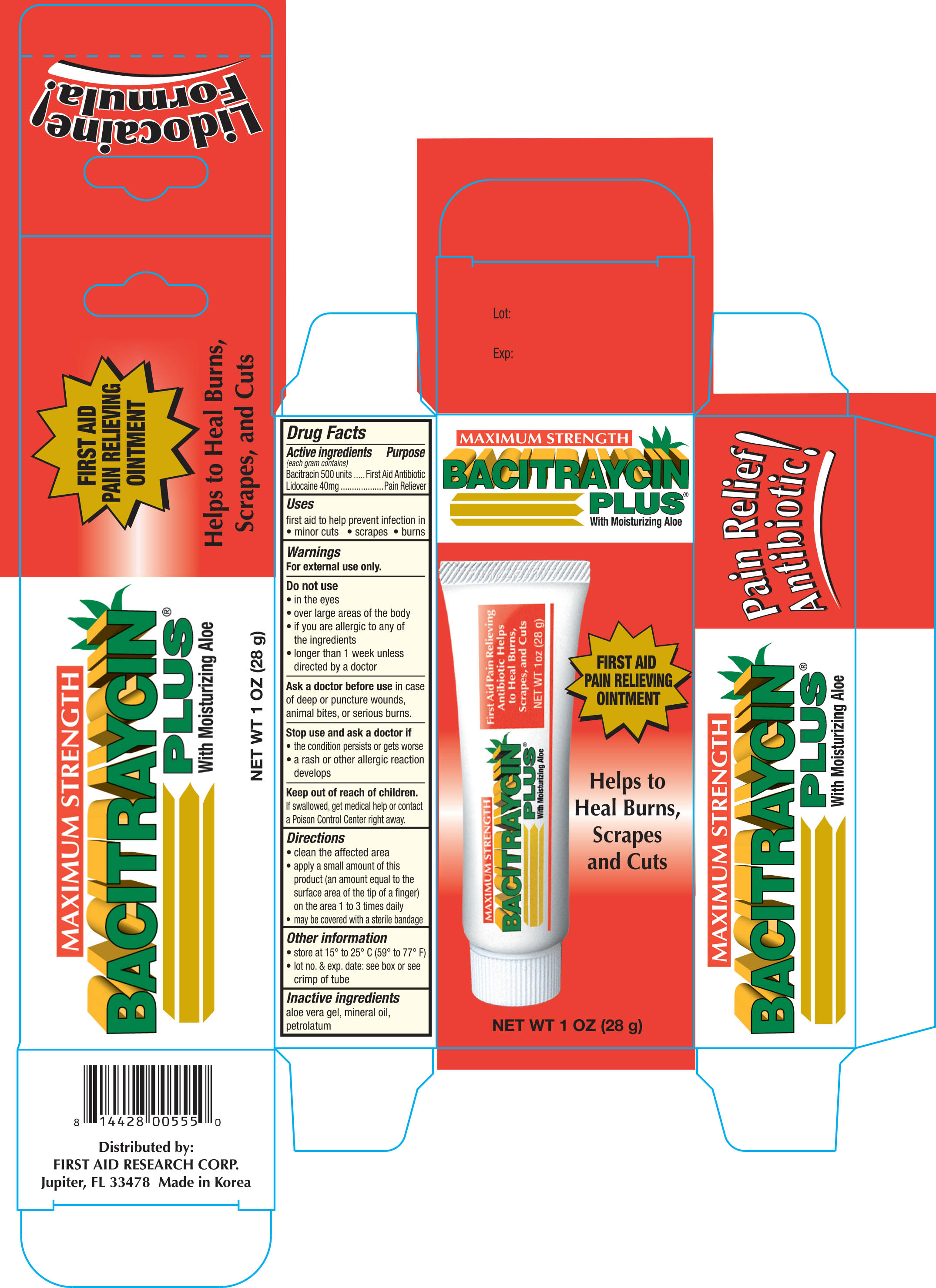 DRUG LABEL: First Aid Research Bacitraycin Plus Maximum Vertical
NDC: 75983-555 | Form: OINTMENT
Manufacturer: First Aid Research Corp.
Category: otc | Type: HUMAN OTC DRUG LABEL
Date: 20170511

ACTIVE INGREDIENTS: BACITRACIN 500 [USP'U]/1 g; LIDOCAINE 40 mg/1 g
INACTIVE INGREDIENTS: ALOE VERA LEAF; MINERAL OIL; PETROLATUM

Active ingredients Purpose

Bacitracin 500 unites......................... First Aid Antibiotic

Lidocaine 40 mg............................... Pain Reliever

Uses

First aid to help prevent infection in

- minor cuts
- scrapes burns

Warnings

For external use only

Do not use

- in the eyes
- over large areas of the body
- if you are allergic to any of the ingredients
- longer than 1 week unless directed by a doctor

Ask a doctor before use in case of deep or puncture wounds, animal bites, or serious burns

Stop use and ask a doctor if

- the condition persits or gets worse
- a rash or other allergic reaction develops

Keep out of reach of children.

If swallowed, get medical help or contact a Poision Control Center right away.

Directions

- clean the affected area
- apply a small amount of this product (an amount equal to the surface area of the tip of a finger) on the area 1 to 3 times daily
- may be convered with a sterile bandage

Other information

- Store at 15° to 25°C (59° to 77°F)
- Lot. No. & Exp. Date: see box or see crimp of tube

Inactive ingredients

aloe vera gel, mineral oil, petrolatum

DOSAGE AND ADMINISTRATION

DISTRIBUTED BY:

FIRST AID RESEARCH CORP.

WANTAGH, NY 11793 USA